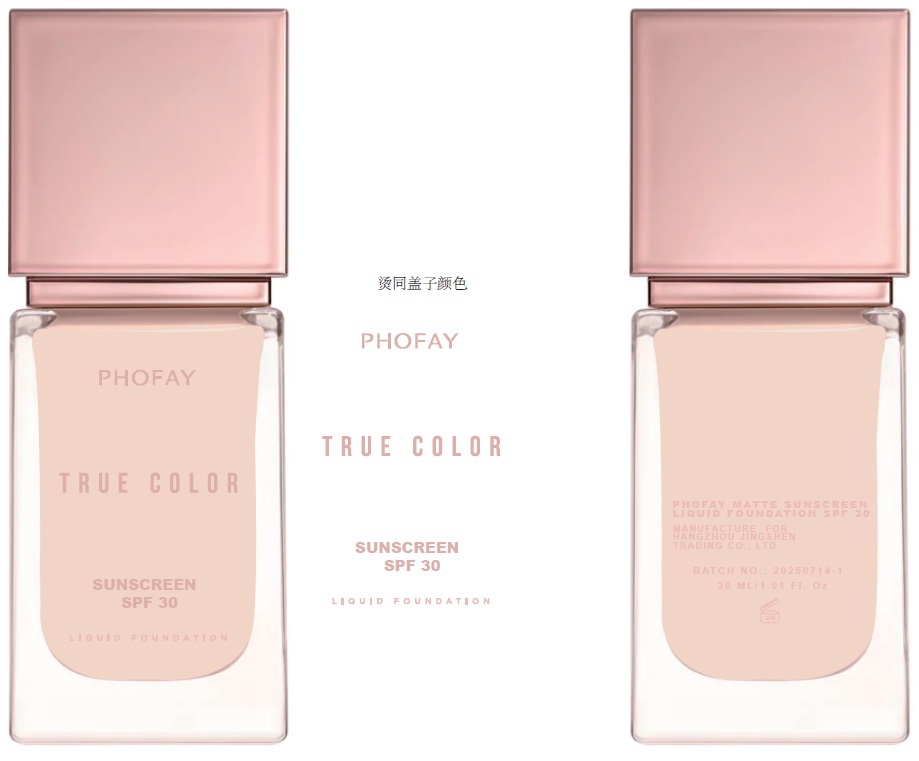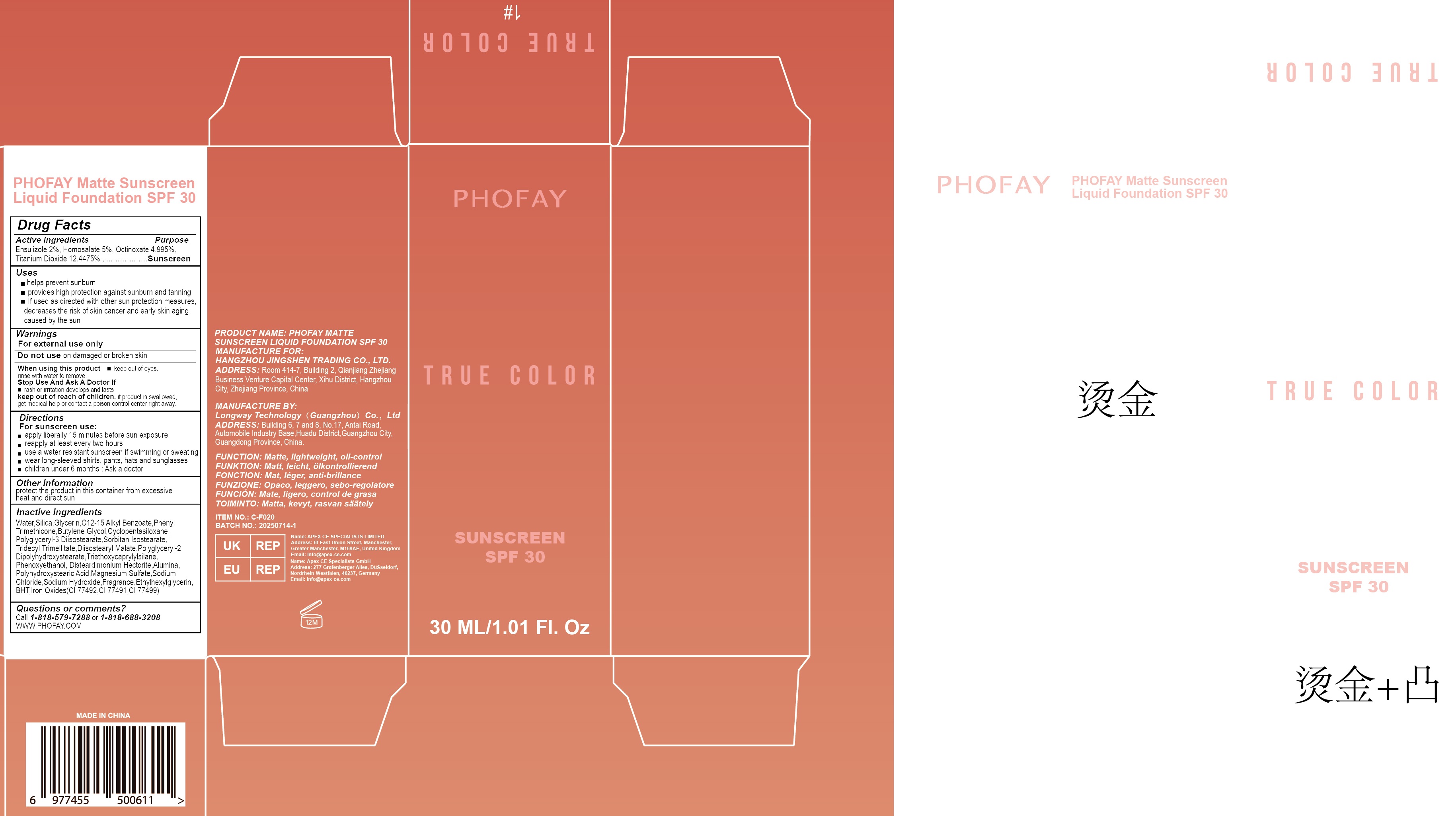 DRUG LABEL: PHOFAY  Matte Sunscreen Liquid Foundation SPF 30, 1
NDC: 87080-000 | Form: LIQUID
Manufacturer: Hangzhou Jingshen Trading Co., Ltd.
Category: otc | Type: HUMAN OTC DRUG LABEL
Date: 20250904

ACTIVE INGREDIENTS: ENSULIZOLE 20 mg/1 mL; HOMOSALATE 50 mg/1 mL; OCTINOXATE 49.95 mg/1 mL; TITANIUM DIOXIDE 124.475 mg/1 mL
INACTIVE INGREDIENTS: WATER; SILICON DIOXIDE; GLYCERIN; C12-15 ALKYL BENZOATE; PHENYL TRIMETHICONE; BUTYLENE GLYCOL; CYCLOMETHICONE 5; POLYGLYCERYL-3 DIISOSTEARATE; SORBITAN ISOSTEARATE; TRIDECYL TRIMELLITATE; DIISOSTEARYL MALATE; POLYGLYCERYL-2 DIPOLYHYDROXYSTEARATE; TRIETHOXYCAPRYLYLSILANE; PHENOXYETHANOL; DISTEARDIMONIUM HECTORITE; ALUMINUM OXIDE; MAGNESIUM SULFATE, UNSPECIFIED FORM; SODIUM CHLORIDE; SODIUM HYDROXIDE; ETHYLHEXYLGLYCERIN; BUTYLATED HYDROXYTOLUENE; FERRIC OXIDE YELLOW; FERRIC OXIDE RED; FERROSOFERRIC OXIDE

PHOFAY Matte Sunscreen Liquid Foundation SPF 30, 1

Active ingredients

Ensulizole 2%, Homosalate 5%, Octinoxate 4.995%, Titanium Dioxide 12.4475%

Purpose

Suscreen

Uses

- helps prevent sunburn
- provides high protection against sunburn and tanning
- lf used as directed with other sun protection measures, decreases the risk of skin cancer and early skin aging caused by the sun

Warnings

For external use only

Do not use

on damaged or broken skin

When using this product

- keep out of eyes. rinse with water to remove.

Stop Use And Ask A Doctor lf

- rash or irritation develops and lasts

keep out of reach if children.

if product is swallowed, get medical help or contact a poison control center right away.

Directions

For sunscreen use:

- apply liberally 15 minutes before sun exposure
- reapply at least every two hours
- use a water resistant sunscreen if swimming or sweating
- wear long-sleeved shirts, pants, hats and sunglasses
- children under 6 months :Ask a doctor

Other information

protect the product in this container from excessive heat and direct sun

Inactive ingredients

Water, Silica, Glycerin, C12-15 Alkyl Benzoate, Phenyl Trimethicone, Butylene Glycol, Cyclopentasiloxane, Polyglyceryl-3 Diisostearate, Sorbitan Isostearate, Tridecyl Trimellitate, Diisostearyl Malate, Polyglyceryl-2 Dipolyhydroxystearate, Triethoxycaprylylsilane, Phenoxyethanol, Disteardimonium Hectorite, Alumina, Polyhydroxystearic Acid, Magnesium Sulfate, Sodium Chloride, Sodium Hydroxide, Fragrance, Ethylhexylglycerin, BHT, lron Oxides (Cl77492, CI 77491, CI 77499)

Questions or comments?

Call 1-818-579-7288or 1-818-688-3208WWW.PHOFAY.COM